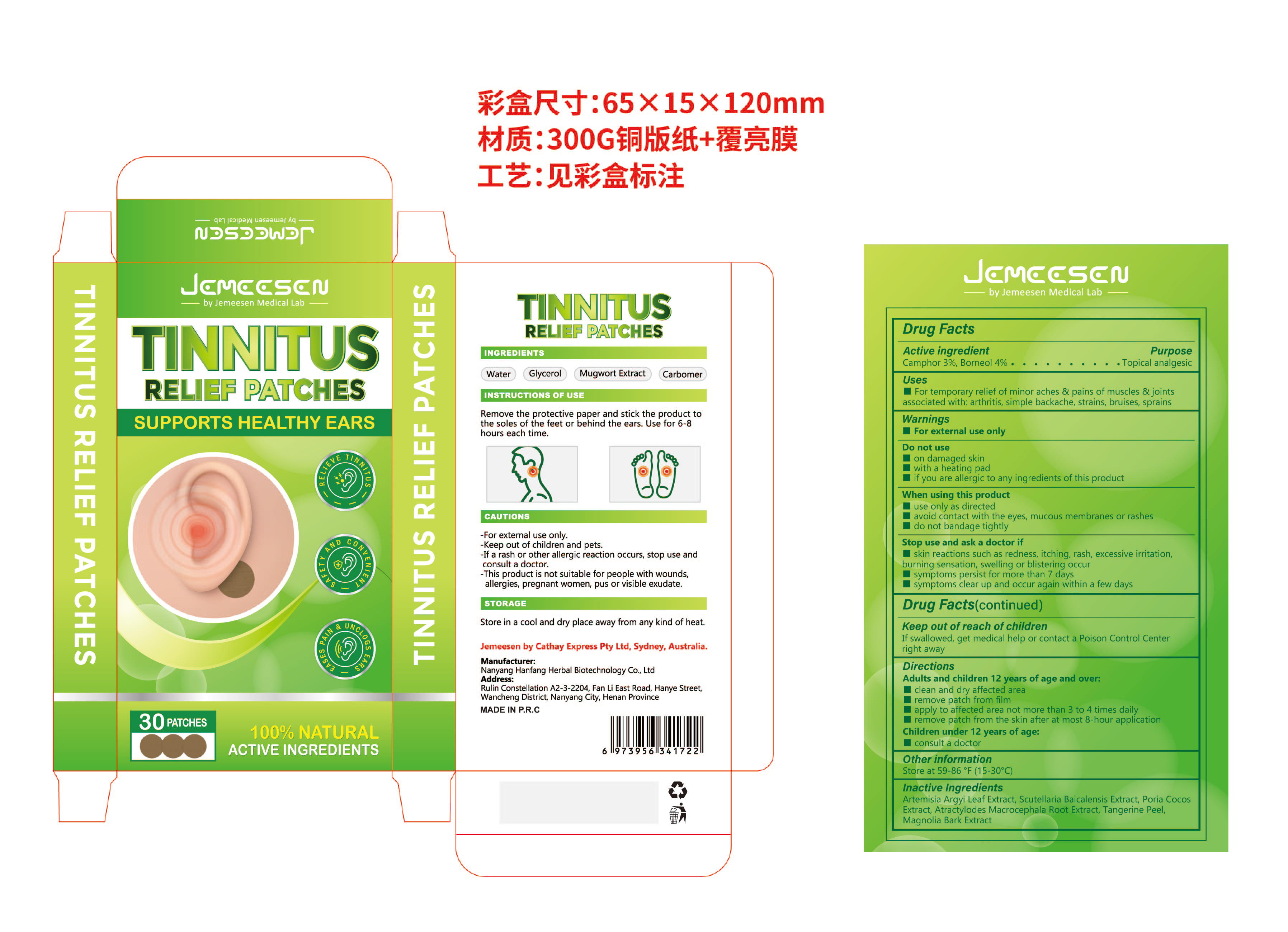 DRUG LABEL: TINNITUS RELINF PATCHES
NDC: 84445-010 | Form: PATCH
Manufacturer: Shenzhen Furuizhilian keji Co., Ltd.
Category: otc | Type: HUMAN OTC DRUG LABEL
Date: 20240807

ACTIVE INGREDIENTS: CAMPHOR, (-)- 0.084 g/28 1; BORNEOL 1.12 g/28 1
INACTIVE INGREDIENTS: ATRACTYLODES MACROCEPHALA ROOT; TANGERINE PEEL; SCUTELLARIA BAICALENSIS ROOT; ARTEMISIA ARGYI LEAF; FU LING; MAGNOLIA OBOVATA BARK

ACTIVE INGREDIENT

Camphor 3%

Borneol 4%

PURPOSE

Topical analgesic

INDICATIONS AND USAGE

For temporary relief of minor aches & pains of muscles & joints associated with: arthritis, simple backache, strains, bruises, sprains

WARNINGS

For external use only

DO NOT USE

on damaged skin
with a heating pad
if you are allergic to any ingredients of this product

WHEN USING

use only as directed
avoid contact with the eyes, mucous membranes or rashes.
do not bandage tightly

STOP USE

■ skin reactions such as redness, itching, rash, excessive irritation,burning sensation, swelling or blistering occur
■ symptoms persist for more than 7 days
■ symptoms clear up and occur again within a few days

KEEP OUT OF REACH OF CHILDREN

If swallowed, get medical help or contact a Poison Control Center right away.

DOSAGE AND ADMINISTRATION

Adults and children 12 years of age and over:
■ clean and dry affected area
■ remove patch from film
■ apply to affected area not more than 3 to 4 times daily
■ remove patch from the skin after at most8-hour application
Children under 12 years of age:
consult a doctor

INACTIVE INGREDIENT

Artemisia Argyi Leaf Extract, Scutellaria Baicalensis Extract, Poria Cocos Extract, Atractylodes Macrocephala Root Extract, Tangerine Peel, Magnolia Bark Extract